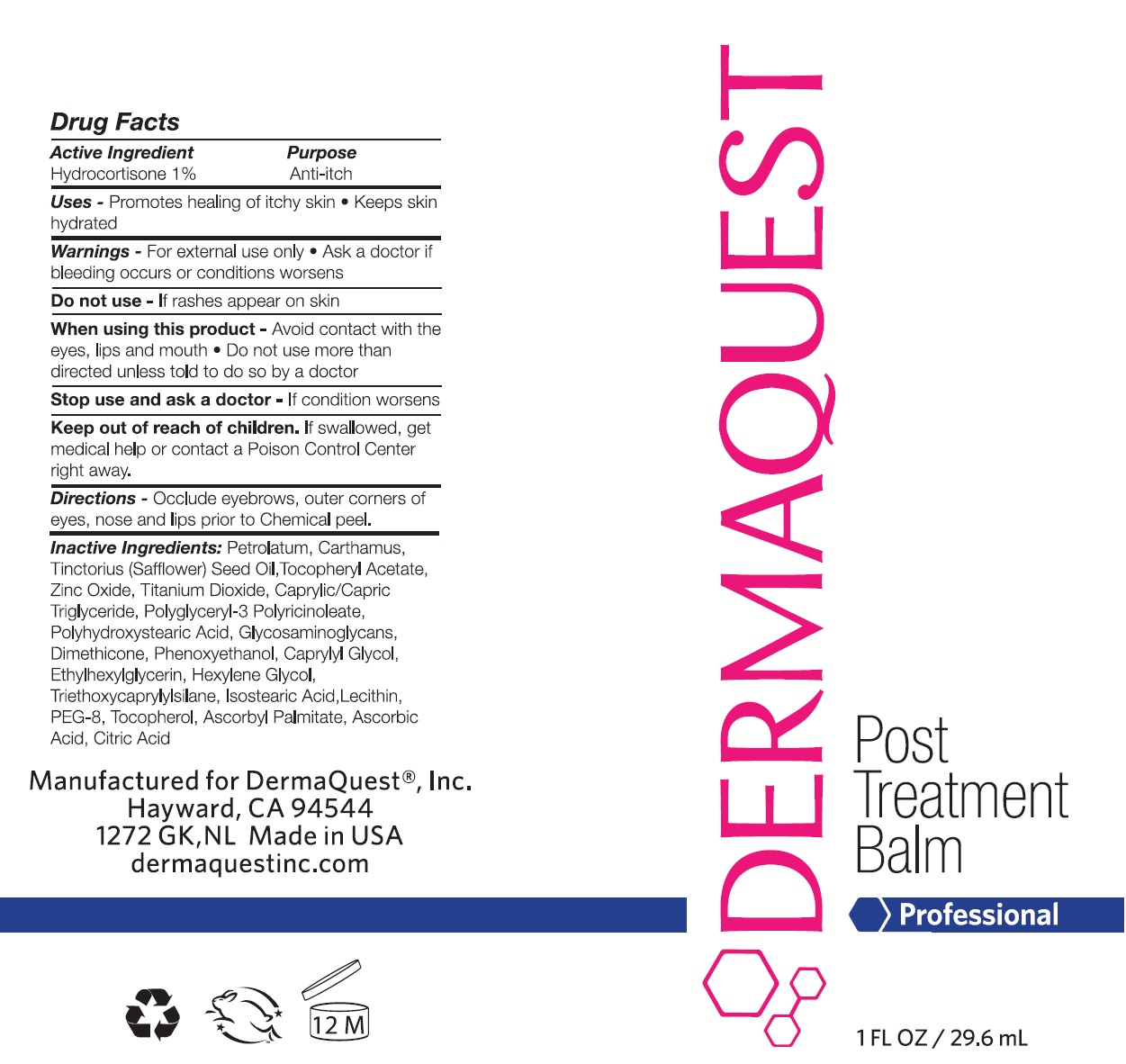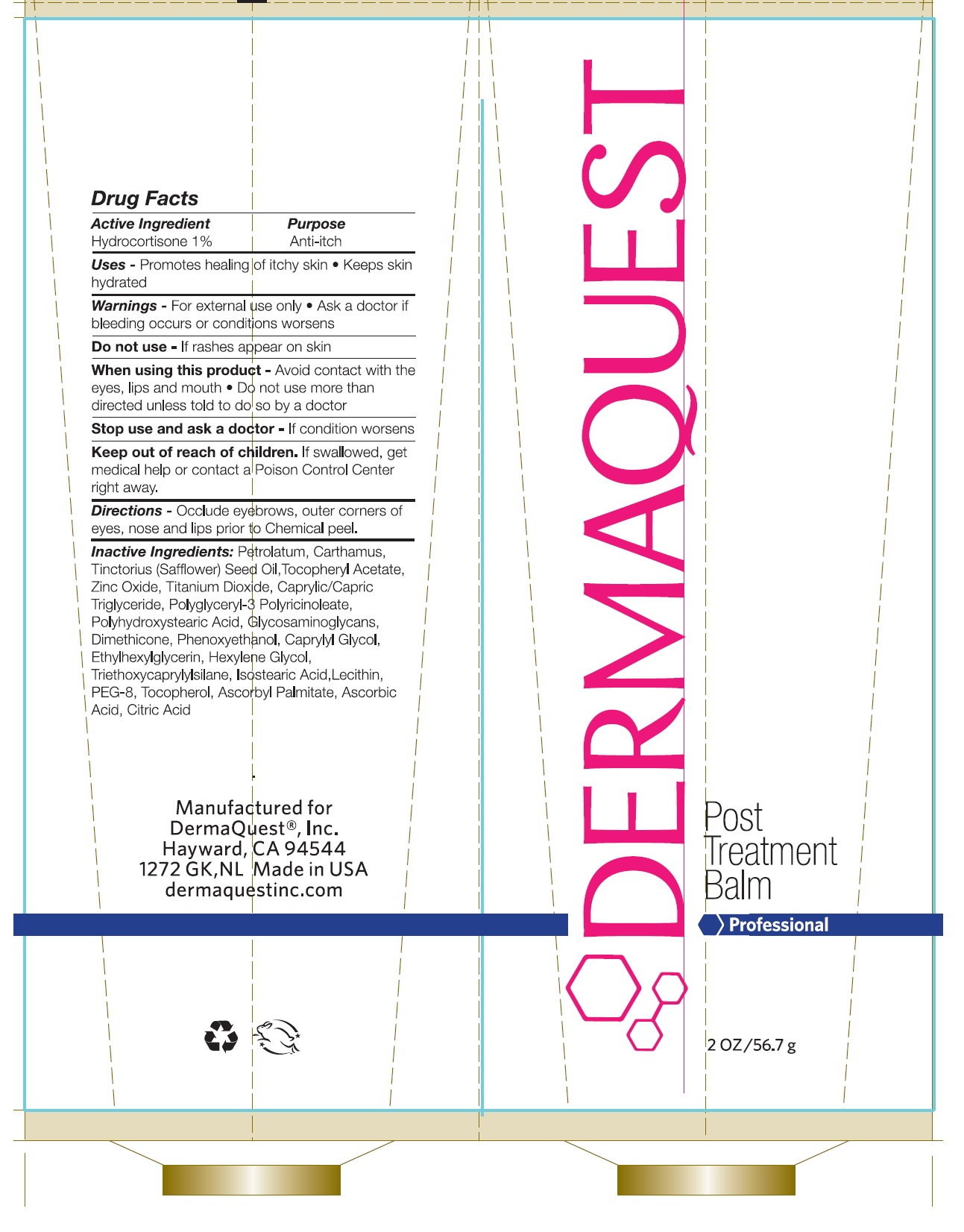 DRUG LABEL: Post Treatment Balm
NDC: 62742-4077 | Form: CREAM
Manufacturer: Allure Labs Inc.
Category: otc | Type: HUMAN OTC DRUG LABEL
Date: 20241205

ACTIVE INGREDIENTS: HYDROCORTISONE 1 mg/1 g
INACTIVE INGREDIENTS: LECITHIN, SOYBEAN; POLYHYDROXYSTEARIC ACID (2300 MW); CITRIC ACID MONOHYDRATE; GAG; ASCORBYL PALMITATE; ASCORBIC ACID; SAFFLOWER; POLYETHYLENE GLYCOL 400; DIMETHICONE; PHENOXYETHANOL; ACETATE ION; MEDIUM-CHAIN TRIGLYCERIDES; TRIETHOXYCAPRYLYLSILANE; ISOSTEARIC ACID; TOCOPHEROL; ETHYLHEXYLGLYCERIN; POLYGLYCERYL-3 PENTARICINOLEATE; TITANIUM DIOXIDE; HEXYLENE GLYCOL; PETROLATUM; SAFFLOWER OIL; ZINC OXIDE

Drug Facts

Active Ingredient: Hydrocortisone 1%

Purpose: Anti-itch

Uses:

- Promotes healing of itchy skin.
- Keeps skin hydrated.

Warnings:

- For external use only.
- Ask a doctor if bleeding occurs or conditions worsens.

Do not use - If rashes appear on skin.

When using this Product:

- Avoid contact with the eyes, lips and mouth.
- Do not use more than directed unless told to do so by a doctor.

Stop use and ask a doctor - If conditions worsens.

Keep out of reach of children:

- If swallowed, get medical help or contact a Poison Control Center right away.

Directions:

- Occlude eyebrows, outer corners of eyes, nose and lips prior to chemical peel.

Inactive Ingredients:

Petrolatum, Carthamus Tinctorius (Safflower) Seed Oil, Tocopheryl Acetate, Zinc Oxide , Titanium Dioxide, Caprylic/Capric Triglyceride, Glyceryl Isostearate, Polyhydroxystearic Acid , Glycosaminoglycans, Dimethicone, Triethoxycaprylylsilane, PEG-8 , Tocopherol , Ascorbyl Palmitate , Ascorbic Acid, Citric Acid

PACKAGE LABEL

Manufactured for DermaQuest®, Inc.

Hayward, CA 94544

1272 GK, NL Made in USA

dermaquestinc.com